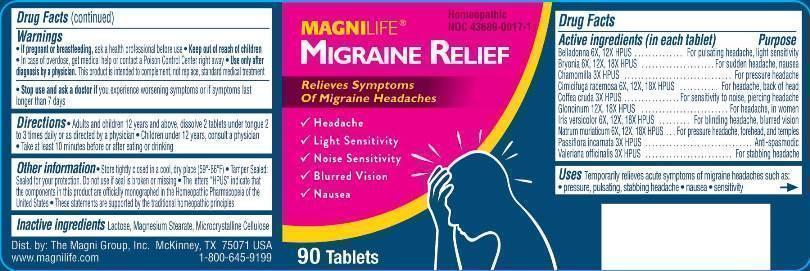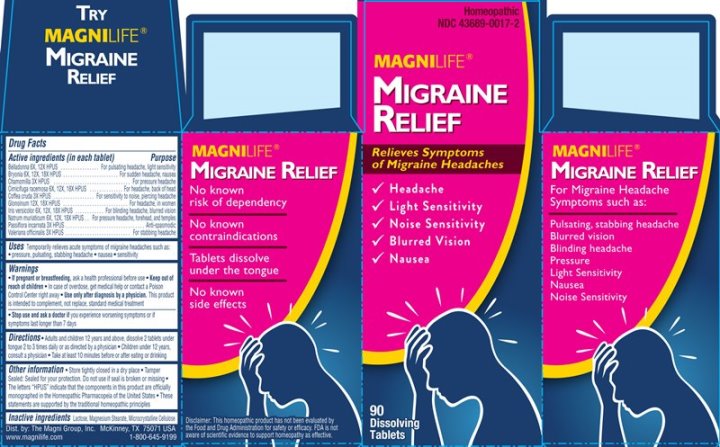 DRUG LABEL: Migraine Relief
NDC: 43689-0017 | Form: TABLET
Manufacturer: The Magni Company
Category: homeopathic | Type: HUMAN OTC DRUG LABEL
Date: 20241105

ACTIVE INGREDIENTS: ATROPA BELLADONNA 6 [hp_X]/1 1; BRYONIA ALBA ROOT 6 [hp_X]/1 1; MATRICARIA CHAMOMILLA WHOLE 3 [hp_X]/1 1; BLACK COHOSH 6 [hp_X]/1 1; ARABICA COFFEE BEAN 3 [hp_X]/1 1; NITROGLYCERIN 12 [hp_X]/1 1; IRIS VERSICOLOR ROOT 6 [hp_X]/1 1; SODIUM CHLORIDE 6 [hp_X]/1 1; PASSIFLORA INCARNATA FLOWERING TOP 3 [hp_X]/1 1; VALERIAN 3 [hp_X]/1 1
INACTIVE INGREDIENTS: LACTOSE; MAGNESIUM STEARATE; CELLULOSE, MICROCRYSTALLINE

DRUG FACTS:

ACTIVE INGREDIENTS:

Belladonna 6X, 12X, Bryonia (Alba) 6X, 12X, 18X, Chamomilla 3X, Cimicifuga Racemosa 6X, 12X, 18X, Coffea Cruda 3X, Glonoinum 12X, 18X, Iris Versicolor 6X, 12X, 18X, Natrum Muriaticum 6X, 12X, 18X, Passiflora Incarnata 3X, Valeriana Officinalis 3X

USES:

Temporarily relieves acute symptoms of migraine headaches such as:

•pressure

•pulsating

•stabbing headache

•nausea

•sensitivity

WARNINGS:

If pregnant or breastfeeding, ask a health professional before use.

Keep out of reach of children. In case of overdose, get medical help or contact a Poison Control Center right away.

Use only after diagnosis by a physician. This product is intended to complement, not replace, proper medical attention.

Stop use and ask a doctor if you experience worsening symptoms or if symptoms last longer than 7 days.

Other Information

Store tightly closed in dry place.

Tamper Sealed: Sealed for your protection. Do not use if seal is broken or missing.

The letters "HPUS" indicate that the components in this product are officially monographed in the Homeopathic

Pharmacopeia of the United States.

These statements are supported by the traditional homeopathic principles.

Keep out of reach of children. In case of overdose, get medical help or contact a Poison Control Center right away.

DIRECTIONS:

Adults and children 12 years and above:

Dissolve 2 tablets under tongue 2 to 3 times daily or as directed by a physician.

Children under 12 years: consult a physician

Take at least 10 minutes before or after eating or drinking.

USES:

Temporarily relieves acute symptoms of migraine headaches such as:

•pressure

•pulsating

•stabbing headache

•nausea

•sensitivity

INACTIVE INGREDIENTS:

Lactose, Magnesium Stearate, Microcrystaline Cellulose.

QUESTIONS:

Dist. by: The Magni Group, Inc. McKinney, TX 75074 USA

www.magnilife.com 1-800-645-9199

PACKAGE LABEL DISPLAY:

MAGNILIFE Homeopathic
NDC 43689-0017-1
MIGRAINE RELIEF

Relieves Symptoms
of Migraine Headaches

√ Headache
√ Light Sensitivity
√ Noise Sensitivity
√ Blurred Vision
√ Nausea

90 Tablets
Dissolving Tablets